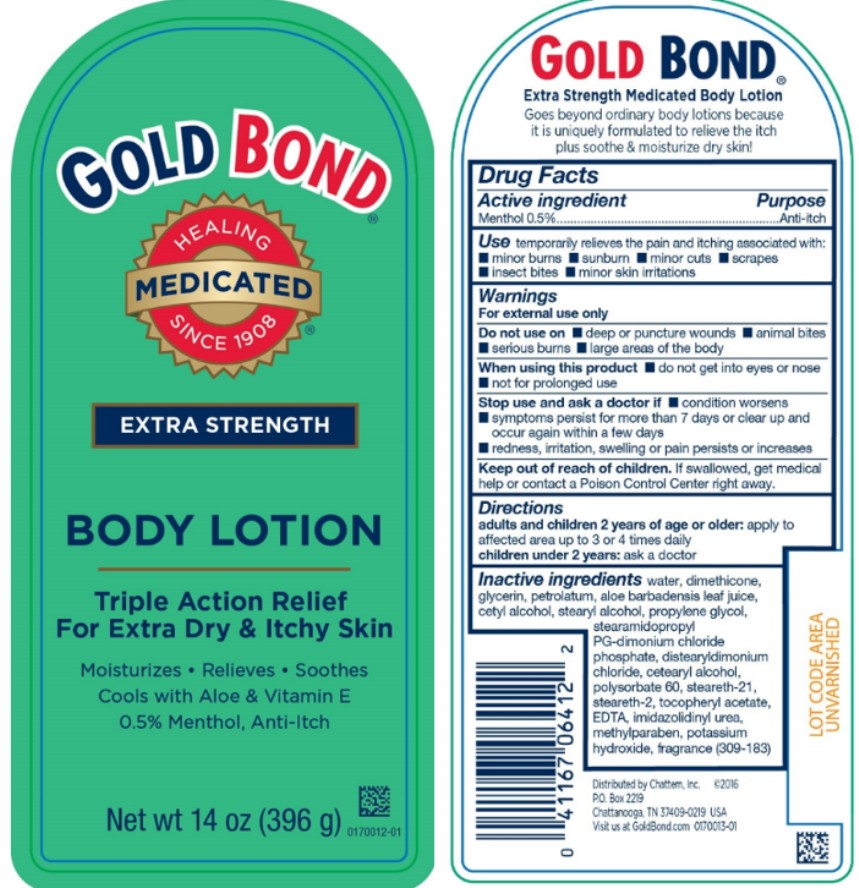 DRUG LABEL: Gold Bond Extra Strength
NDC: 41167-0641 | Form: LOTION
Manufacturer: Chattem, Inc.
Category: otc | Type: HUMAN OTC DRUG LABEL
Date: 20260114

ACTIVE INGREDIENTS: MENTHOL 0.005 g/1 g
INACTIVE INGREDIENTS: WATER; DIMETHICONE; GLYCERIN; PETROLATUM; ALOE VERA LEAF; CETYL ALCOHOL; STEARYL ALCOHOL; PROPYLENE GLYCOL; STEARAMIDOPROPYL PG-DIMONIUM CHLORIDE PHOSPHATE; DISTEARYLDIMONIUM CHLORIDE; CETOSTEARYL ALCOHOL; POLYSORBATE 60; STEARETH-21; STEARETH-2; .ALPHA.-TOCOPHEROL ACETATE, D-; EDETATE DISODIUM; IMIDUREA; METHYLPARABEN; POTASSIUM HYDROXIDE

Gold Bond Medicated Extra Strength Lotion

Drug Facts – Extra Strength Gold Bond Body Lotion

Active ingredients

Menthol 0.5%

Purpose

Anti-itch

Uses

temporarily relieves the pain and itching associated with:

- minor skin irritations
- minor burns
- minor cuts
- insect bites
- sunburn
- scrapes

Warnings

For external use only

Do not use on

- deep or puncture wounds
- animal bites
- serious burns
- large areas of the body

When using this product

- do not get into eyes or nose
- not for prolonged use

Stop use and ask a doctor if

- condition worsens
- symptoms persist for more than 7 days or clear up and occur again within a few days
- redness, irritation, swelling or pain persists or increases

Keep out of reach of children.

If swallowed, get medical help or contact a Poison Control Center right away.

Directions

adults and children 2 years and older: apply to affected area up to 3 or 4 times daily

children under 2 years: ask a doctor

Inactive ingredients

water, dimethicone, glycerin, petrolatum, aloe barbadensis leaf juice, cetyl alcohol, stearyl alcohol, propylene glycol, stearamidopropyl PG-dimonium chloride phosphate, distearyldimonium chloride, cetearyl alcohol, polysorbate 60, steareth-21, steareth-2, tocopheryl acetate, EDTA, imidazolidinyl urea, methylparaben, potassium hydroxide, fragrance

PRINCIPAL DISPLAY PANEL

GOLD BOND®
EXTRA STRENGTH
BODY LOTION
Triple Action Relief
For Extra Dry & Itchy Skin
Net wt 14 oz (396 g)